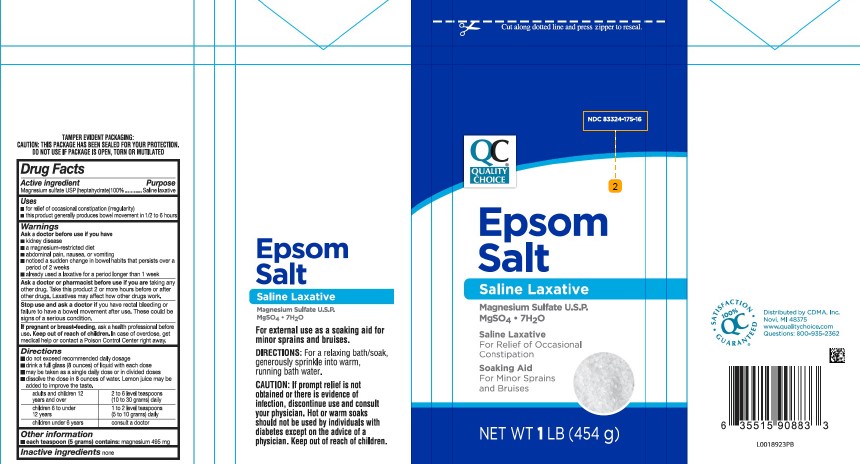 DRUG LABEL: Epsom Salt
NDC: 83324-175 | Form: GRANULE, FOR SOLUTION
Manufacturer: Chain Drug Marketing Association
Category: otc | Type: HUMAN OTC DRUG LABEL
Date: 20260227

ACTIVE INGREDIENTS: MAGNESIUM SULFATE HEPTAHYDRATE 1 g/1 g

Quality Choice 602.002/602AA
Epsom Salt

Tamper Evident Statement

TAMPER EVIDENT PACKAGING:

CAUTION: THIS PACKAGE HAS BEEN SEALED FOR YOUR PROTECTION.

DO NOT USE IF PACKAGE IS OPEN, TORN OR MUTILATED.

Active ingredient

Magnesium sulfate USP (Heptahydrate) 100%

Purpose

Saline laxative

Uses

- for relief of occasional constipation (irregularity)
- this product generally produces bowel movement in 1/2 to 6 hours

Warnings

for this product

Ask a doctor before use if you have

- kidney disease
- a magnesium-restricted diet
- abdominal pain, nausea or vomiting
- noticed a sudden change in bowel habits that persists over a period of 2 weeks
- already used a laxative for a period longer than 1 week.

Ask a doctor or pharmacist before use if you are

taking any other drug. Take this product 2 or more hours before or after other drugs. Laxatives may affect how other drugs work.

Stop use and ask a doctor

you have rectal bleeding or failure to have a bowel movement after use. These could be signs of a serious condition.

If pregnant or breast-feeding

ask a health professional before use.

Keep out of reach of children

In case of overdose, get medical help or contact a Poison Control Center right away.

Directions

- do not exceed recommended daily dosage
- drink a full glass (8 ounces) of liquid with each dose
- may be taken as a single daily dose or in divided doses
- dissolve the dose in 8 ounces of water. Lemon juice may be added to improve the taste.

adults and children 12 years and over - 2 to 6 level teaspoons (10 to 30 grams) daily

children 6 to under 12 years - 1 to 2 level teaspoons (5 to 10 grams) daily

children under 6 years - consult a doctor

Other information

- each teaspoon (5 grams) contains: magnesium 495 mg

Inactive ingredient

None

Claims

Epsom Salt

Saline Laxitive

Magnesium Sulfate U.S.P.

MgSO4 • 7H2O

For external use as a soaking for minor sprains and bruises.

Directions: For a relaxing bath/soak, generously sprinkle Epsom Salt into warm, running bath water.

CAUTION: If prompt relief is not obtained or there is evidence of infection, discontinue use and consult your physician. Hot or warm soaks should not be used by individuals with diabetes except on the advice of a physician. Keep out of reach of children.

Adverse reaction

SATISFACTION GUARANTEED

100% QC

Distributed By:CDMA, Inc.

Novi, MI 48375

www. qualitychoice.com

Questions: 800-935-2362

Principal display panel

Cut along dotted line and press zipper to reseal.

NDC 83324-175-16

QC®

QUALITY

CHOICE

Epsom

Salt

Saline Laxative

Magnesium Sulfate U.S.P.

MgSO4 • 7H2O

Saline Laxative

For Relief of Occasional Constipation

Soaking Aid

For Minor Sprains and Bruises

NET WT 1 LB (454 g)